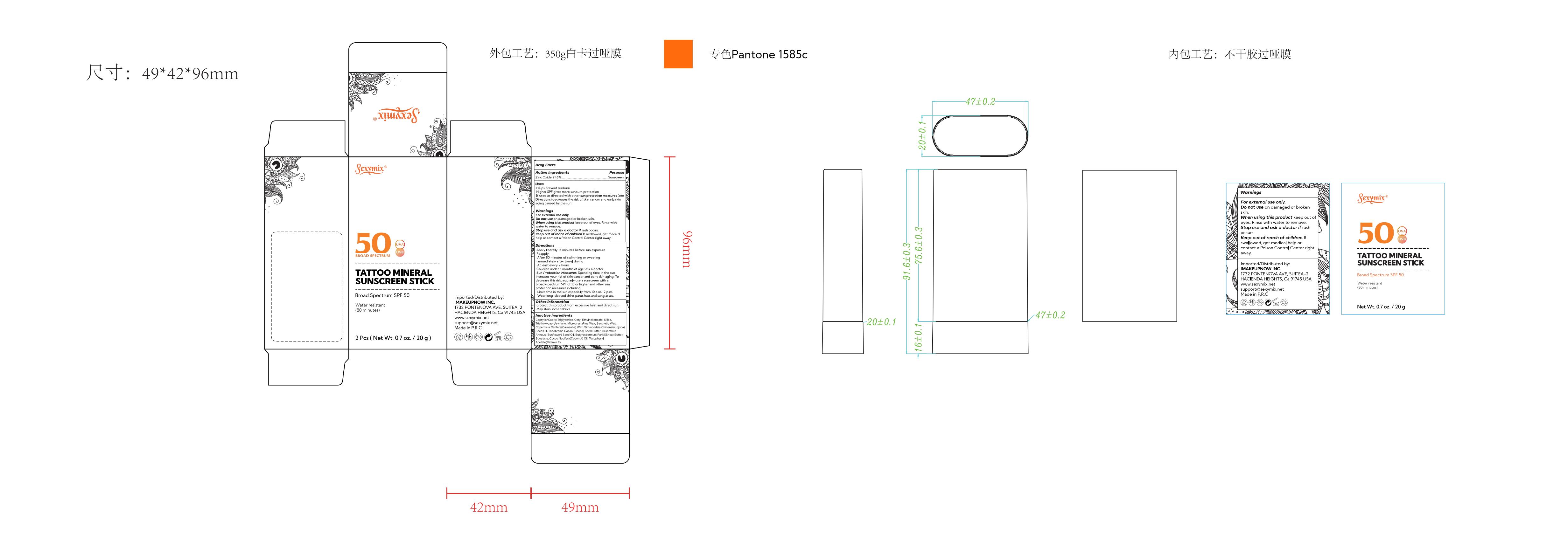 DRUG LABEL: SEXY MIX Tattoo Mineral Sunscreen Stick Broad Spectrum SPF 50
NDC: 82723-004 | Form: STICK
Manufacturer: Aopline Health Industry Technology (Guangzhou) Co., Ltd.
Category: otc | Type: HUMAN OTC DRUG LABEL
Date: 20250108

ACTIVE INGREDIENTS: ZINC OXIDE 21.6 g/100 g
INACTIVE INGREDIENTS: ALPHA-TOCOPHEROL ACETATE; MEDIUM-CHAIN TRIGLYCERIDES; CETYL ETHYLHEXANOATE; TRIETHOXYCAPRYLYLSILANE; MICROCRYSTALLINE WAX; SUNFLOWER OIL; SHEA BUTTER; SILICON DIOXIDE; SQUALANE; COCONUT OIL; JOJOBA OIL; COCOA BUTTER; CARNAUBA WAX; SYNTHETIC WAX (1200 MW)

82723-004
SEXY MIX Tattoo Mineral Sunscreen Stick Broad Spectrum SPF 50

Active Ingredients

Zinc Oxide 21.6%
Titanium Dioxide 23.9%

Purpose

purpose: sunscreen

Uses

Helps prevent sunburn
Higher SPF gives more sunburn protection
If used as directed with other sun protection measures (see
Directions) , decreases the risk of skin cancer and early skin
aging caused by the sun

Warnings

For external use only .
Do not use on damaged or broken skin
When using this product keep out of eyes . Rinse with
water to remove
Stop use and ask a doctor if rash occurs
Keep out of reach of children . If swallowed , get medical
help or contact a Poison Control Center right away .

Directions

Apply liberally 15 minutes before sun exposure
Reappl.
After 80 minutes of swimming or sweating
Immediately after towel drying
At least every 2 hours-
Children under 6 months of age . ask a doctor-
Sun Protection Measures . Spending time in the sun
increases your risk of skin cancer and early skin agng . To
decrease this risk , regularly use a sunscreen with a
broad-spectrum SPF of 15 or higher and other sun
protection measures including
Limit time in the sun , especially from 10 a.m. -2 p m.
Wear long-sleeved shirts , pants , hats , and sunglasses

Other Information

protect this product from excessive heat and direct sun
May stain some fabrics

Inactive Ingredients

Inactive ingredient
Caprylic / Capric Triglyceride , Cetyl Ethylhexanoate , Silica ,
TriethoxycaprylIylsilane , Microcrystalline Wax , Synthetic Wax ,
Copernicia Cerifera (Carnauba) Wax , Simmondsia Chinensis (Jojoba)
Seed Oil , Theobroma Cacao (Cocoa) Seed Butter , Helianthus
Annuus (Sunflower) Seed Oil , Butyrospermum Parki Shea) Butter ,
Squalane , Cocos Nucifera (Coconut) Oil , Tocopheryl
Acetate (Vitamin E)

Keep out of reach of children . If swallowed , get medical
help or contact a Poison Control Center right away .

Stop use

When using this product keep out of eyes . Rinse with
water to remove
Stop use and ask a doctor if rash occurs
Keep out of reach of children . If swallowed , get medical
help or contact a Poison Control Center right away .

When using this product keep out of eyes . Rinse with
water to remove
Stop use and ask a doctor if rash occurs
Keep out of reach of children . If swallowed , get medical
help or contact a Poison Control Center right away .

Do not use on damaged or broken skin
When using this product keep out of eyes . Rinse with
water to remove
Stop use and ask a doctor if rash occurs
Keep out of reach of children . If swallowed , get medical
help or contact a Poison Control Center right away .

Package Label

82723-004 TATTOO MINERAL SUNSCREEN STICK